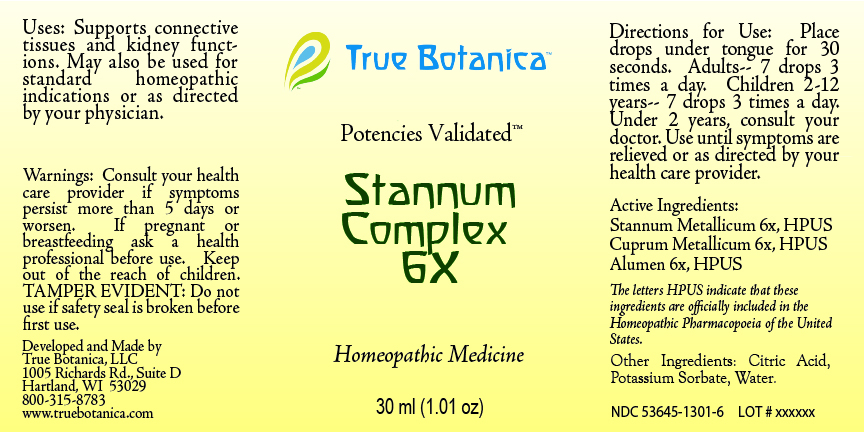 DRUG LABEL: Stannum Complex 6X
NDC: 53645-1301 | Form: LIQUID
Manufacturer: True Botanica, LLC
Category: homeopathic | Type: HUMAN OTC DRUG LABEL
Date: 20260219

ACTIVE INGREDIENTS: COPPER 6 [hp_X]/30 mL; POTASSIUM ALUM 6 [hp_X]/30 mL; TIN 6 [hp_X]/30 mL
INACTIVE INGREDIENTS: POTASSIUM SORBATE; CITRIC ACID MONOHYDRATE; WATER

Stannum Complex 6X

ACTIVE INGREDIENT

Stannum Metallicum 6X

Cuprum Metallicum 6X

Alumen 6X

PURPOSE

Supports connective tissues and kidney functions. May also be use for standard homeopathic indications or as directed by your physician.

Use:

Supports connective tissues and kidney functions. May also be use for standard homeopathic indications or as directed by your physician.

Warnings:

Consult your health care provider if symptoms persist more than 5 days or worsen.

PREGNANCY OR BREAST FEEDING

If pregnant or breastfeeding ask a health professional before use.

Keep out of the reach of children.

DO NOT USE

TAMPER EVIDENT: Do not use if safety seal is broken before first use.

Directions for Use:

Place drops under tongue for 30 seconds. Adults 7 drops 3 times a day. Children 2-12 years, 7 drops 3 times a day. Under 2 years, consult your doctor. Use until symptoms are relieved or as directed by your health care provider.

Other Ingredients:

Citric Acid, Potassium Sorbate, Water

QUESTIONS

Developed and Made by

True Botanica, LLC

1005 Richards Rd., Suite D

Hartland, WI 53029

800-315-8783

www.truebotanica.com